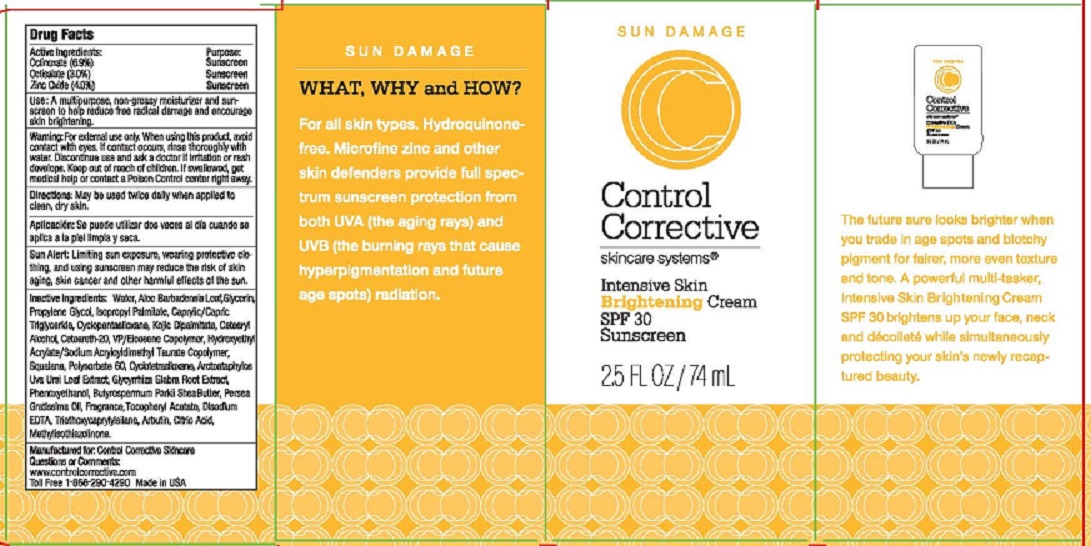 DRUG LABEL: CONTROL CORRECTIVE INTENSIVE SKIN BRIGHTENING
NDC: 70764-205 | Form: CREAM
Manufacturer: CONTROL CORRECTIVE SKINCARE INC
Category: otc | Type: HUMAN OTC DRUG LABEL
Date: 20251231

ACTIVE INGREDIENTS: OCTINOXATE 6.9 g/100 mL; OCTISALATE 3 g/100 mL; ZINC OXIDE 4 g/100 mL
INACTIVE INGREDIENTS: WATER; ALOE VERA LEAF; GLYCERIN; PROPYLENE GLYCOL; ISOPROPYL PALMITATE; MEDIUM-CHAIN TRIGLYCERIDES; CYCLOMETHICONE 5; KOJIC DIPALMITATE; CETOSTEARYL ALCOHOL; POLYOXYL 20 CETOSTEARYL ETHER; VINYLPYRROLIDONE/EICOSENE COPOLYMER; HYDROXYETHYL ACRYLATE/SODIUM ACRYLOYLDIMETHYL TAURATE COPOLYMER (45000 MPA.S AT 1%); SQUALANE; POLYSORBATE 60; CYCLOMETHICONE 4; ARCTOSTAPHYLOS UVA-URSI LEAF; GLYCYRRHIZA INFLATA ROOT; PHENOXYETHANOL; SHEA BUTTER; AVOCADO OIL; .ALPHA.-TOCOPHEROL ACETATE; EDETATE DISODIUM; TRIETHOXYCAPRYLYLSILANE; ARBUTIN; ANHYDROUS CITRIC ACID; METHYLISOTHIAZOLINONE

CONTROL CORRECTIVE INTENSIVE SKIN BRIGHTENING CREAM SPF 30 SUNSCREEN (70764-205)

ACTIVE INGREDIENTS

OCTINOXATE (6.9%)

OCTISALATE (3.0%)

ZINC OXIDE (4.0%)

PURPOSE

SUNSCREEN

USE

A MULTI-PURPOSE , NON-GREASY MOISTURIZER AND SUNSCREEN TO HELP REDUCE FREE RADICAL DAMAGE AND ENCOURAGE SKIN BRIGHTENING.

WARNING

FOR EXTERNAL USE ONLY. WHEN USING THIS PRODUCT, AVOID CONTACT WITH EYES. IF CONTACT OCCURS, RINSE THOROUGHLY WITH WATER. DISCONTINUE USE AND ASK A DOCTOR IF IRRITATION OR RASH DEVELOPS.

DIRECTIONS

MAY BE USED TWICE DAILY WHEN APPLIED TO CLEAN, DRY SKIN.

OTHER SAFETY INFORMATION

SUN ALERT: LIMITING SUN EXPOSURE, WEARING PROTECTIVE CLOTHING, AND USING SUNSCREEN MAY REDUCE THE RISK OF SKIN AGING, SKIN CANCER, AND OTHER HARMFUL EFFECTS OF THE SUN.

INACTIVE INGREDIENTS

WATER, ALOE BARBADENSIS LEAF, GLYCERIN, PROPYLENE GLYCOL, ISOPROPYL PALMITATE, CAPRYLIC/CAPRIC TRIGLYCERIDES, CYCLOPENTASILOXANE, KOJIC DIPALMITATE, CETEARYL ALCOHOL, CETEARETH-20, VP/EICOSENE COPOLYMER, HYDROXYETHYL ACRYLATE/SODIUM ACRYLOYLDIMETHYL TAURATE COPOLYMER, SQUALANE, POLYSORBATE 60, CYCLOTETRASILOXANE, ARCTOSTAPHYLOS UVA URSI LEAF EXTRACT, GLYCYRRHIZA GLABRA ROOT EXTRACT, PHENOXYETHANOL, BUTYROSPERMUM PARKII SHEA BUTTER, PERSEA GRATISSIMA OIL, FRAGRANCE, TOCOPHERYL ACETATE, DISODIUM EDTA, TRIETHOXYCAPRYLYLSILANE, ARBUTIN, CITRIC ACID, METHYLISOTHIAZOLINONE

KEEP OUT OF REACH OF CHILDREN. IF SWALLOWED, GET MEDICAL HELP OR CONTACT A POISON CONTROL CENTER RIGHT AWAY.

QUESTIONS OR COMMENTS:

WWW.CONTROLCORRECTIVE.COM

TOLL FREE 1-866-290-4290 MADE IN USA